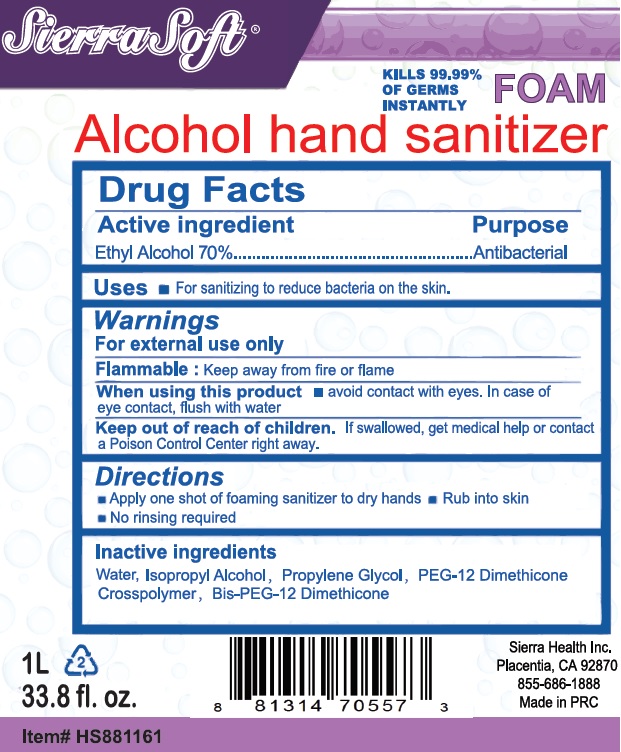 DRUG LABEL: Sierra Soft Alcohol Hand Sanitizer
NDC: 70415-100 | Form: LIQUID
Manufacturer: CWGC LA Inc.
Category: otc | Type: HUMAN OTC DRUG LABEL
Date: 20250417

ACTIVE INGREDIENTS: ALCOHOL 700 mg/1 mL
INACTIVE INGREDIENTS: WATER; ISOPROPYL ALCOHOL; PROPYLENE GLYCOL

CWGC (as PLD) - Sierra Soft Alcohol Hand Sanitizer Foam (70415-100)

Active ingredient

Ethyl Alcohol 70%

Purpose

Antibacterial

Uses

- For sanitizing to reduce bacteria on the skin.

Warnings

For external use only

Flammable:

Keep away from fire or flame

When using this product

- avoid contact with eyes. In case of eye contact, flush with water

Keep out of reach of children.

If swallowed, get medical help or contact a Poison Control Center right away.

Directions

• Apply one shot of foaming sanitizer to dry hands • Rub into skin • No rinsing required

Inactive ingredients

Water, Isopropyl Alcohol, Propylene Glycol, PEG-12 Dimethicone Crosspolymer, Bis-PEG-12 Dimethicone